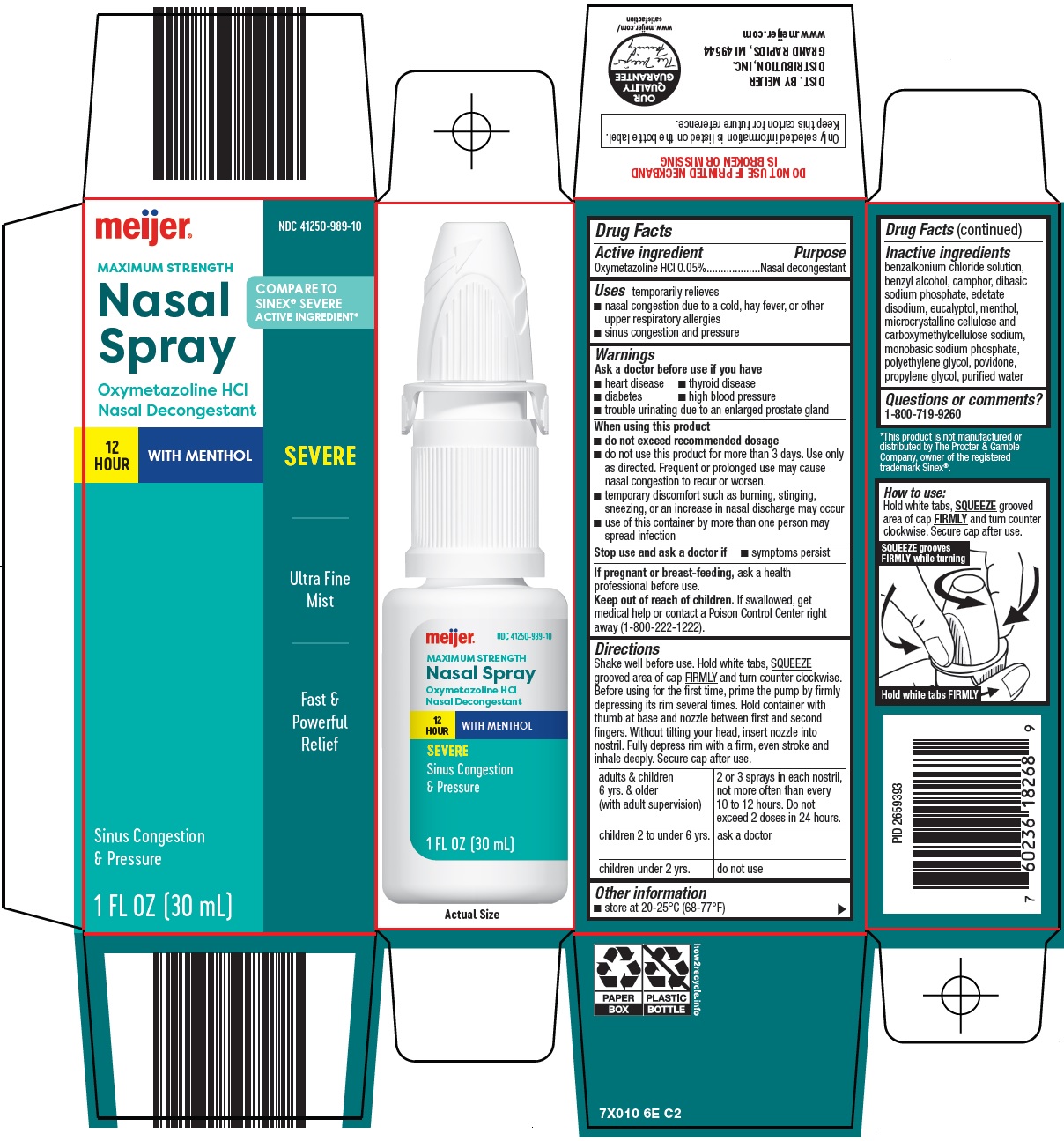 DRUG LABEL: nasal
NDC: 41250-989 | Form: SPRAY
Manufacturer: Meijer Distribution Inc
Category: otc | Type: HUMAN OTC DRUG LABEL
Date: 20241113

ACTIVE INGREDIENTS: OXYMETAZOLINE HYDROCHLORIDE 0.05 g/100 mL
INACTIVE INGREDIENTS: BENZALKONIUM CHLORIDE; BENZYL ALCOHOL; SODIUM PHOSPHATE, DIBASIC, UNSPECIFIED FORM; EDETATE DISODIUM; EUCALYPTOL; MENTHOL, UNSPECIFIED FORM; MICROCRYSTALLINE CELLULOSE; CARBOXYMETHYLCELLULOSE SODIUM, UNSPECIFIED; SODIUM PHOSPHATE, MONOBASIC, UNSPECIFIED FORM; POLYETHYLENE GLYCOL, UNSPECIFIED; POVIDONE, UNSPECIFIED; PROPYLENE GLYCOL; WATER

Meijer Distribution, Inc. Nasal Spray Drug Facts

Active ingredient

Oxymetazoline HCl 0.05%

Purpose

Nasal decongestant

Uses

temporarily relieves

- nasal congestion due to a cold, hay fever, or other upper respiratory allergies
- sinus congestion and pressure

Ask a doctor before use if you have

- heart disease
- thyroid disease
- diabetes
- high blood pressure
- trouble urinating due to an enlarged prostate gland

When using this product

- do not exceed recommended dosage
- do not use this product for more than 3 days. Use only as directed. Frequent or prolonged use may cause nasal congestion to recur or worsen.
- temporary discomfort such as burning, stinging, sneezing, or an increase in nasal discharge may occur
- use of this container by more than one person may spread infection

Stop use and ask a doctor if

- symptoms persist

If pregnant or breast feeding,

ask a health professional before use.

Keep out of reach of children

If swallowed, get medical help or contact a Poison Control Center right away (1-800-222-1222).

Directions

Shake well before use. Hold white tabs, SQUEEZE grooved area of cap FIRMLY and turn counter clockwise. Before using for the first time, prime the pump by firmly depressing its rim several times. Hold container with thumb at base and nozzle between first and second fingers. Without tilting your head, insert nozzle into nostril. Fully depress rim with a firm, even stroke and inhale deeply. Secure cap after use.

adults & children 6 yrs. & older (with adult supervision) | 2 or 3 sprays in each nostril, not more often than every 10 to 12 hours. Do not exceed 2 doses in 24 hours.
children 2 to under 6 yrs | ask a doctor
children under 2 yrs | do not use

Other information

- store at 20-25°C (68-77°F)

Inactive ingredients

benzalkonium chloride solution, benzyl alcohol, camphor, dibasic sodium phosphate, edetate disodium, eucalyptol, menthol, microcrystalline cellulose and carboxymethylcellulose sodium, monobasic sodium phosphate, polyethylene glycol, povidone, propylene glycol, purified water

Questions or comments?

1-800-719-9260

PACKAGE/LABEL PRINCIPAL DISPLAY PANEL

Meijer®

MAXIMUM STRENGTH

Nasal Spray

COMPARE TO SINEX® SEVERE ACTIVE INGREDIENT

Oxymetazoline HCl

Nasal Decongestant

12 HOUR

WITH MENTHOL

SEVERE

Ultra Fine Mist

Fast & Powerful Relief

Sinus Congestion & Pressure

1 FL OZ (30 mL)